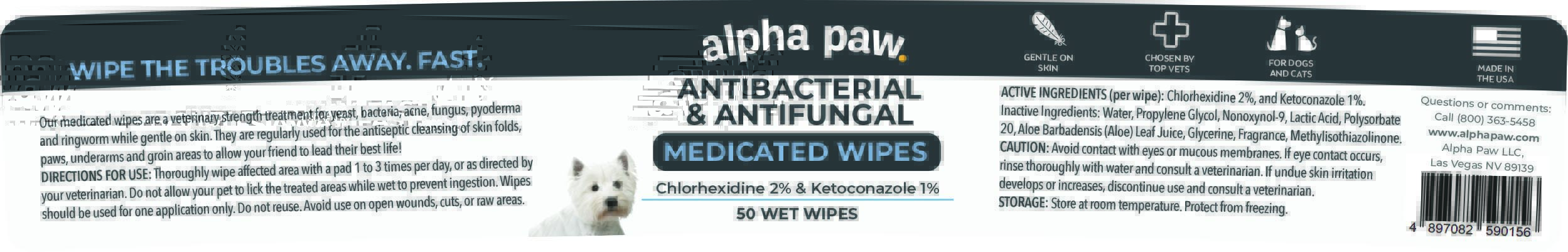 DRUG LABEL: ANTIBACTERIAL ANTIFUNGAL MEDICATED WIPES
NDC: 86175-001 | Form: CLOTH
Manufacturer: Alpha Paw Inc
Category: animal | Type: OTC ANIMAL DRUG LABEL
Date: 20230323

ACTIVE INGREDIENTS: CHLORHEXIDINE 2 g/100 g; KETOCONAZOLE 1 g/100 g
INACTIVE INGREDIENTS: WATER; PROPYLENE GLYCOL; NONOXYNOL-9; LACTIC ACID, UNSPECIFIED FORM; POLYSORBATE 20; GLYCERIN; ALOE VERA LEAF; METHYLISOTHIAZOLINONE

ANTIBACTERIAL & ANTIFUNGAL MEDICATED WIPES

ACTIVE INGREDIENTS (per wipe)

Chlorhexidine 2%, and Ketoconazole 1%.

PURPOSE

ANTIBACTERIAL & ANTIFUNGAL MEDICATED WIPES

INDICATIONS AND USAGE

Our medicated wipes are a veterinary strength treatment for yeast, bacteria, acne, fungus, pyoderma and ringworm while gentle on skin. They are regularly used for the antiseptic cleansing of skin folds, paws, underarms and groin areas to allow your friend to lead their best life!

INACTIVE INGREDIENTS

Water, Propylene Glycol, Nonoxynol-9, Lactic Acid, Polysorbate 20, Aloe Barbadensis (Aloe) Leaf Juice, Glycerine, Fragrance, Methylisothiazolinone.

CAUTION

Avoid contact with eyes or mucous membranes. If eye contact occurs, rinse thoroughly with water and consult a veterinarian. If undue skin irritation develops or increases, discontinue use and consult a veterinarian.

DIRECTIONS

Thoroughly wipe affected area with a pad 1 to 3 times per day, or as directed by your veterinarian. Do not allow your pet to lick the treated areas while wet to prevent ingestion. Wipes should be used for one application only. Do not reuse. Avoid use on open wounds, cuts, or raw areas.

STORAGE

Store at room temperature. Protect from freezing

Chlorhexidine 2% & Ketoconazole 1%

50 WET WIPES

WIPE THE TROUBLES AWAY. FAST.

GENTLE ON SKIN
CHOSEN BY TOP VETS
FOR DOGS AND CATS

ALPHA PAW
Questions or Comments:
Call (800) 363-5458
www.alphapaw.com
Alpha Paw LLC, Las Vegas NV 89139

Packaging

Package 50 Wipes